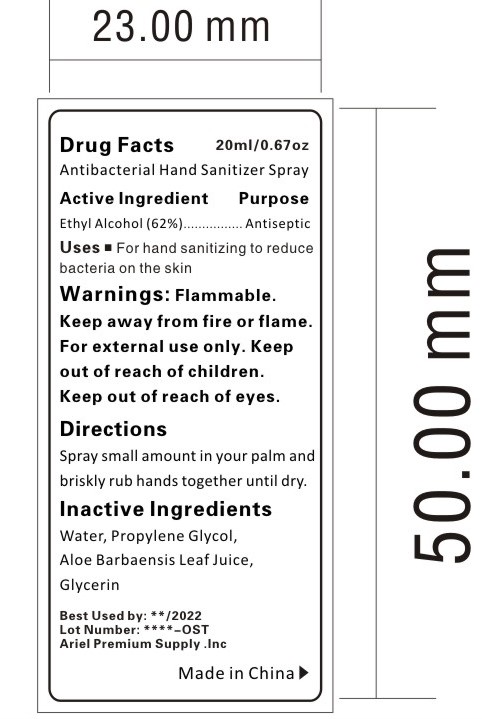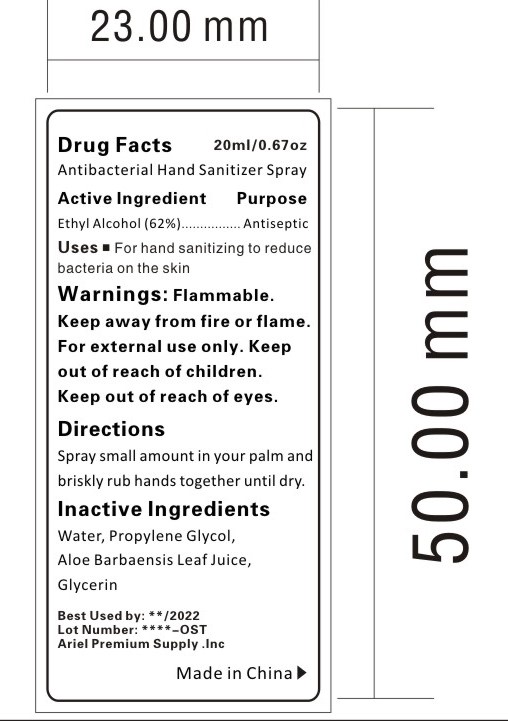 DRUG LABEL: ANTIBACTERIAL HAND SANITIZERSPRAY
NDC: 47993-303 | Form: GEL
Manufacturer: NINGBO JIANGBEI OCEAN STAR TRADING CO.,LTD
Category: otc | Type: HUMAN OTC DRUG LABEL
Date: 20201105

ACTIVE INGREDIENTS: ALCOHOL 62 g/112 mL
INACTIVE INGREDIENTS: WATER; PROPYLENE GLYCOL; ALOE VERA LEAF; GLYCERIN

47993-303

Active ingredients

Ethyl Alcohol (62%)

PURPOSE

Antiseptic

Uses：

For hand sanitizing to reduce bacteria on the skin.

Warnings:

Flammable. Keep away from fire or flame.For external use only.

Keep out of reach of children.

WHEN USING

Keep out of reach of eyes.

Directions:

Squeeze small amount in your palm and briskly rub hands together until dry.

Inactive Ingredients:

Water,Propylene Glycol,Aloe Barbaensis Leaf Juice,Glycerin